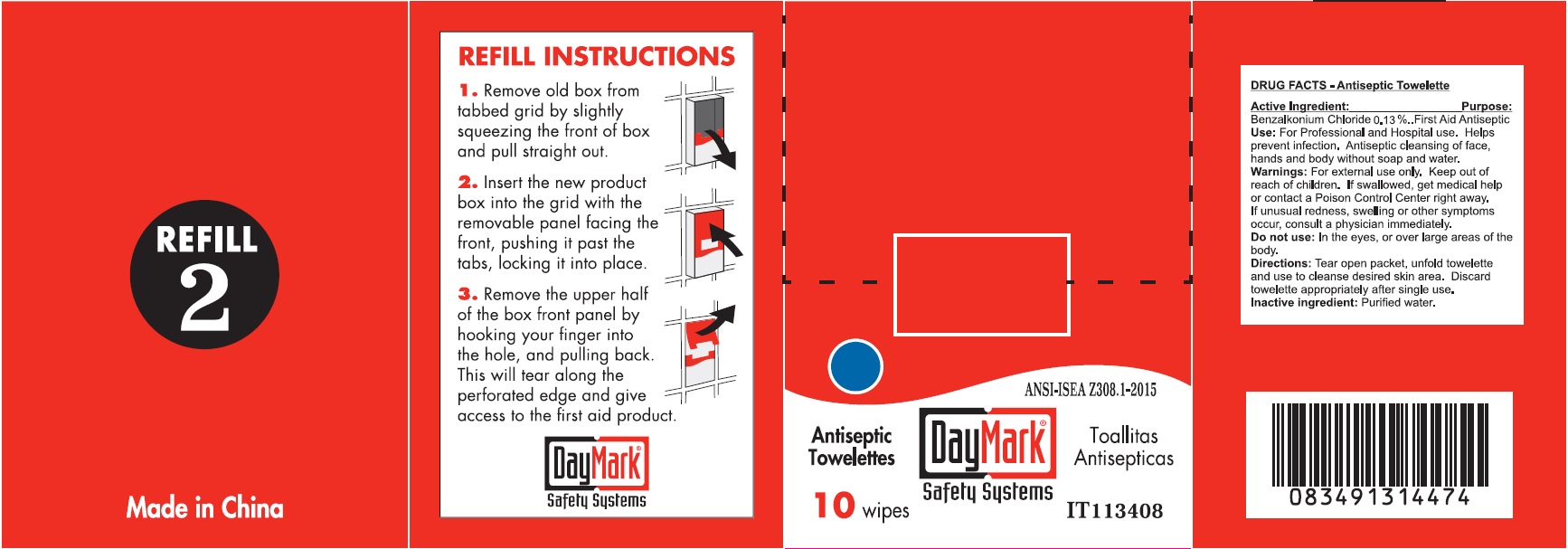 DRUG LABEL: Antiseptic Towelettes
NDC: 49687-0011 | Form: CLOTH
Manufacturer: CMC Group Inc.
Category: otc | Type: HUMAN OTC DRUG LABEL
Date: 20250113

ACTIVE INGREDIENTS: BENZALKONIUM CHLORIDE 0.13 g/100 g
INACTIVE INGREDIENTS: WATER

Antiseptic Towelettes

Active Ingredient:

Benzalkonium Chloride 0.13%

Purpose:

First Aid Antiseptic

Use:

For Professional and Hospital use. Helps prevent infection. Antiseptic cleansing of face, hands and body without soap and water.

Warnings:

For external use only.

Keep out of reach of children.

If swallowed, get medical help or contact a Poison Control Center right away. If unusual redness, swelling or other symptoms occur, consult a physician immediately.

Do not use:

In the eyes, or over large areas of the body.

Directions:

Tear open packet, unfold towelette and use to cleanse desired skin area. Discard towelette appropriately after single use.

Inactive ingredient:

Purified water.